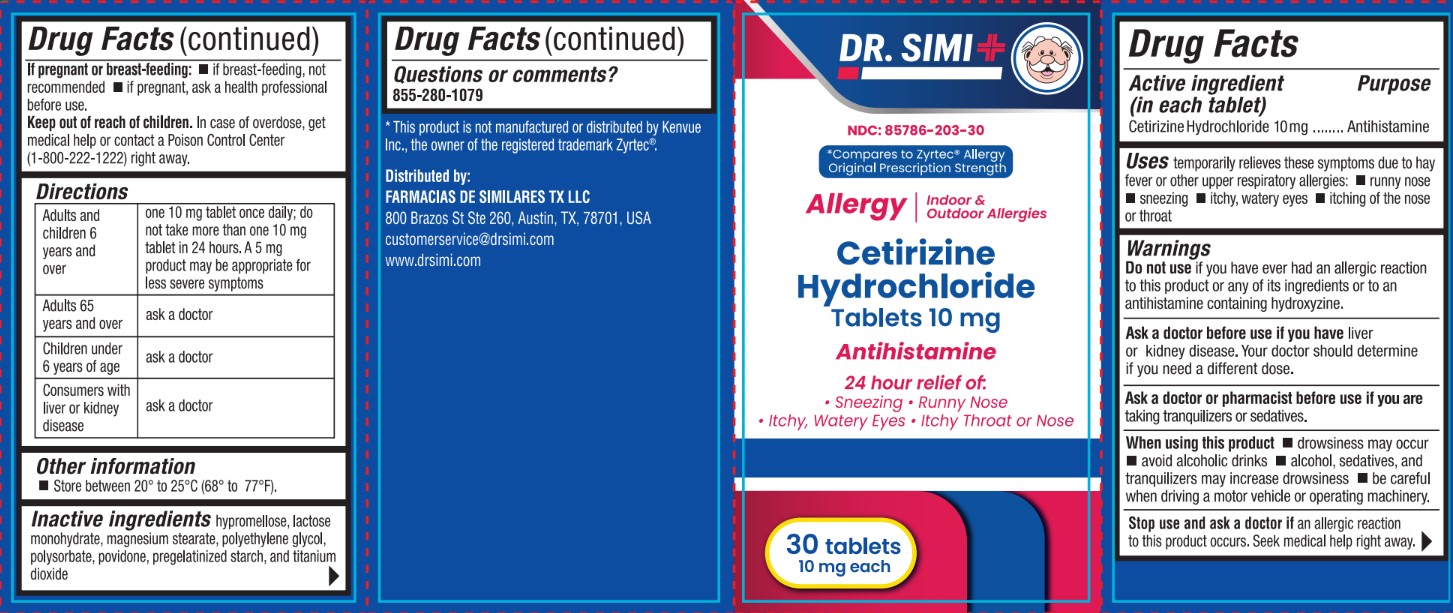 DRUG LABEL: Dr Simi Cetirizine Hydrochloride 10 mg
NDC: 85786-203 | Form: TABLET, FILM COATED
Manufacturer: Farmacias De Similares TX LLC
Category: otc | Type: HUMAN OTC DRUG LABEL
Date: 20260120

ACTIVE INGREDIENTS: CETIRIZINE HYDROCHLORIDE 10 mg/1 1
INACTIVE INGREDIENTS: STARCH, CORN; TITANIUM DIOXIDE; HYPROMELLOSES; POLYSORBATE 80; POVIDONE K30; POLYETHYLENE GLYCOL 400; MAGNESIUM STEARATE; LACTOSE MONOHYDRATE

Active Ingredient (in each tablet)

Cetirizine Hydrochloride 10 mg

Purpose

Antihistamine

Uses

Temporarily relieves these symptoms due to hay fever or other upper respiratory allergies:

- runny nose
- sneezing
- itchy, watery eyes
- itching of the nose or throat

Warnings

Do not use

if you have ever had an allergic reaction to this product or any of its ingredients or to an antihistamine containing hydroxyzine.

Ask a doctor before use if you have

if you have liver or kidney disease. Your doctor should determine if you need a different dose.

Ask a doctor or pharmacist before use

if you are taking tranquilizers or sedatives.

When using this product

- drowsiness may occur
- avoid alcoholic drinks
- alcohol, sedatives, and tranquilizers may increase drowsiness
- be careful when driving a motor vehicle or operating machinery.

Stop use and ask a doctor

if an allergic reaction to this product occurs. Seek medical help right away.

If pregnant or breast feeding

- if breastfeeding, not recommended
- if pregnant, ask a health professional before use.

Keep out of reach of children

Overdosage

In case of overdose, get medical help or contact a Poison Control Center (1-800-222-1222) right away.

Directions

Adults and children 6 years and over:
one 10 mg tablet once daily; do not take more than one 10 mg tablet in 24 hours. A 5 mg product may be appropriate for less severe symptoms

Adults 65 years and over:
ask a doctor

Children under 6 years of age:
ask a doctor

Consumers with liver or kidney disease:
ask a doctor

Other information

Store between 20° to 25°C (68° to 77°F)

Inactive ingredients

hypromellose, lactose monohydrate, magnesium stearate, polyethylene glycol, polysorbate, povidone, pregelatinized starch, and titanium dioxide

Questions or comments?

855-280-1079

* This product is not manufactured or distributed by Kenvue Inc., the owner of the registered trademark Zyrtec®.

Distributed by:
FARMACIAS DE SIMILARES TX LLC
800 Brazos St Ste 260, Austin, TX, 78701, USA
customerservice@drsimi.com
www.drsimi.com

PACKAGE LABEL

NDC: 85786-203-30

*Compares to Zyrtec® Allergy Original Prescription Strength

Allergy | Indoor & Outdoor Allergies

Cetirizine Hydrochloride
Tablets 10 mg

Antihistamine

24 hour relief of:
· Sneezing

· Runny Nose
· Itchy, Watery Eyes

· Itchy Throat or Nose

30 tablets

10 mg each